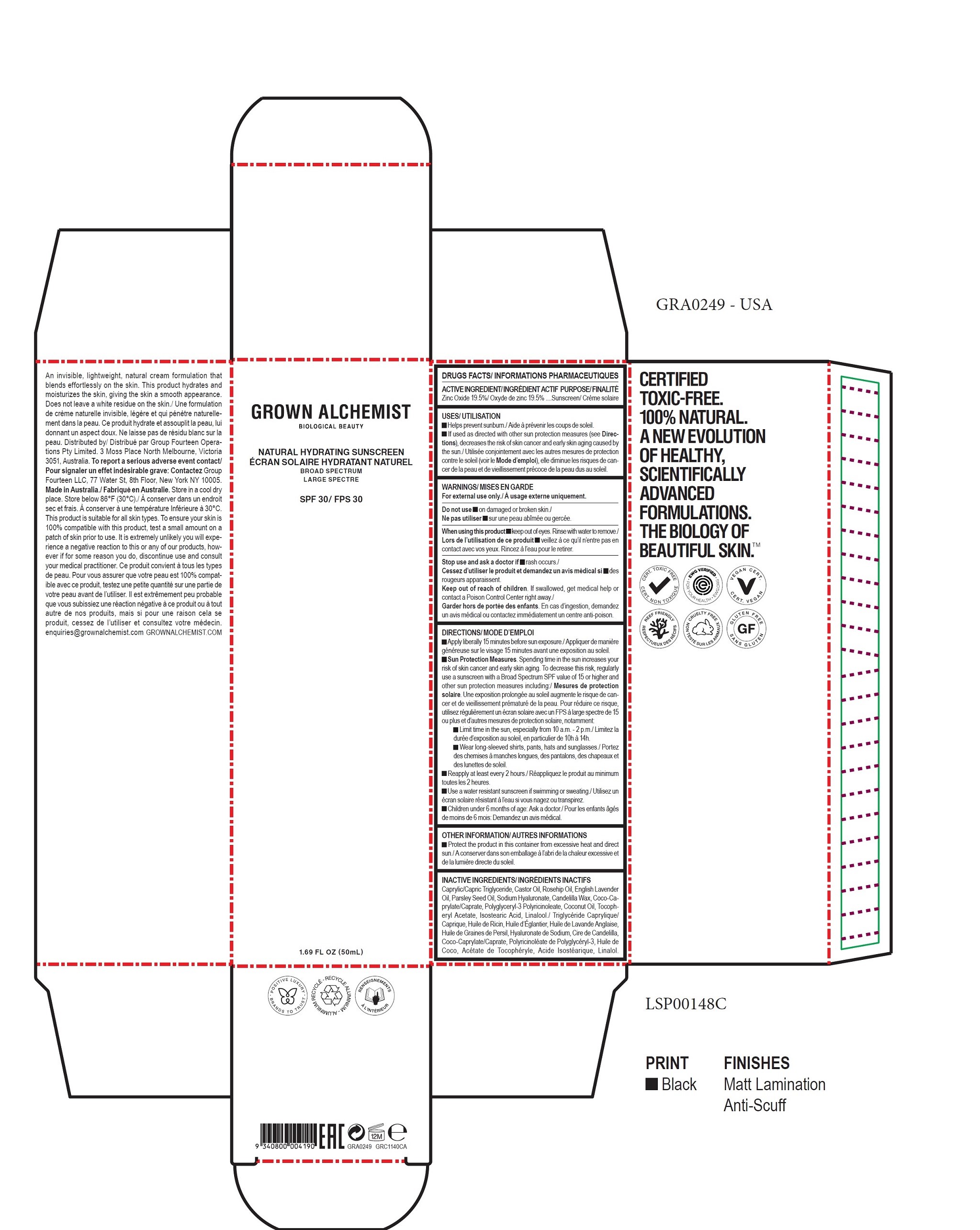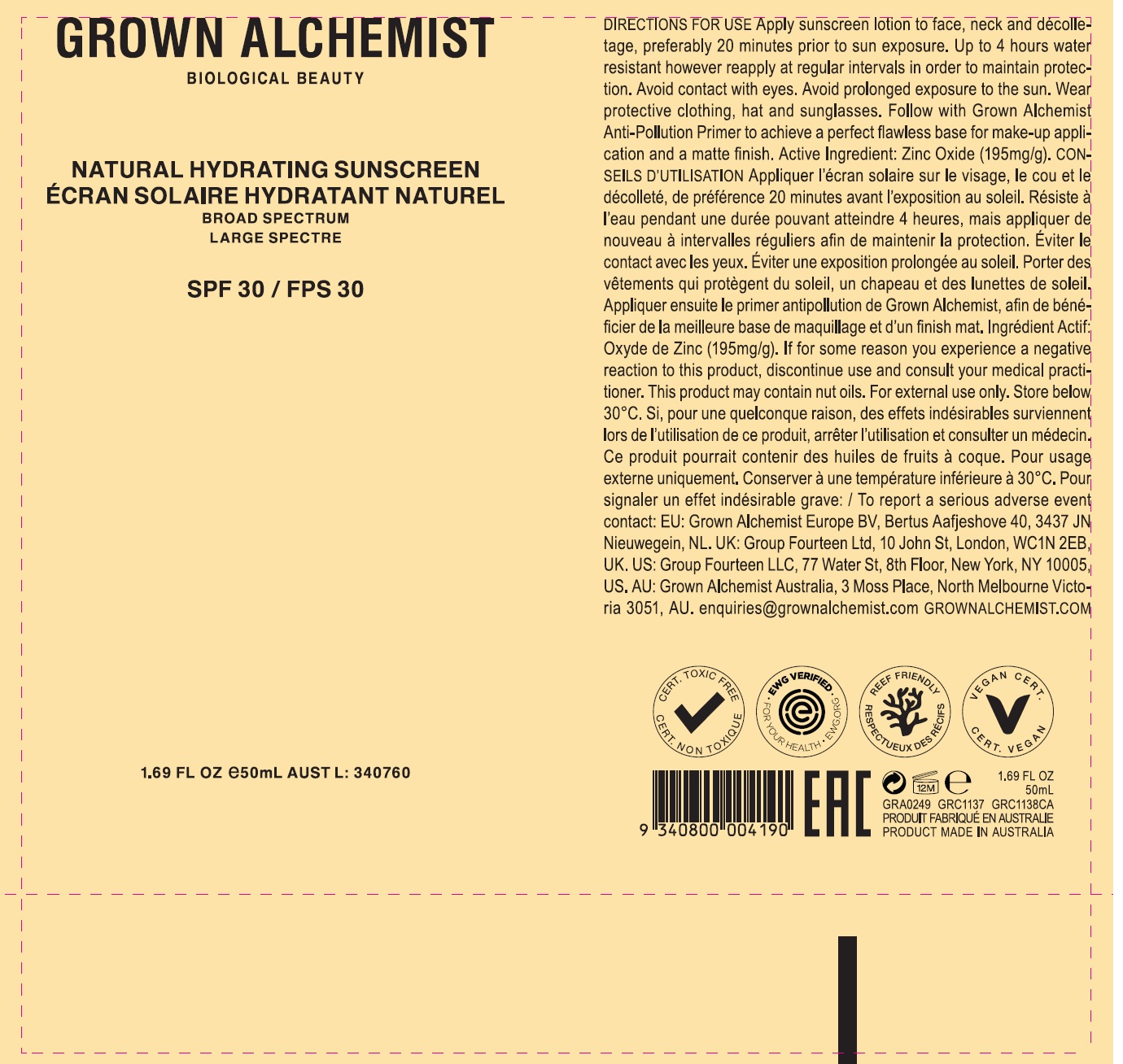 DRUG LABEL: Natural Hydrating Shield SPF 30
NDC: 79228-0000 | Form: CREAM
Manufacturer: Group Fourteen Operations Pty Limited
Category: otc | Type: HUMAN OTC DRUG LABEL
Date: 20231221

ACTIVE INGREDIENTS: ZINC OXIDE 195 mg/1 mL
INACTIVE INGREDIENTS: MEDIUM-CHAIN TRIGLYCERIDES; CASTOR OIL; ROSA CANINA FRUIT OIL; ENGLISH LAVENDER OIL; PARSLEY SEED OIL; HYALURONATE SODIUM; CANDELILLA WAX; COCOYL CAPRYLOCAPRATE; POLYGLYCERYL-3 PENTARICINOLEATE; COCONUT OIL; .ALPHA.-TOCOPHEROL ACETATE; ISOSTEARIC ACID; LINALOOL, (+/-)-

Natural Hydrating Shield SPF 30

ACTIVE INGREDIENT

Zinc Oxide 19.5%

PURPOSE

Sunscreen

USES

- Helps prevent sunburn.
- If used as directed with other sun protection measures (see Directions), decreases the risk of skin cancer and early skin aging caused by the sun.

WARNINGS

For external use only.

Do not use

- on damaged or broken skin.

When using this product

- keep out of eyes. Rinse with water to remove.

Stop use and ask a doctor if

- rash occurs.

Keep out of reach of children.

If swallowed, get medical help or contact a Poison Control Center right away.

DIRECTIONS

- Apply liberally 15 minutes before sun exposure.
- Sun Protection Measures. Spending time in the sun increases your risk of skin cancer and early skin aging. To decrease this risk, regularly
  use a sunscreen with a Broad Spectrum SPF value of 15 or higher and other sun protection measures including:
- Limit time in the sun, especially from 10 a.m. - 2 p.m.
- Wear long-sleeved shirts, pants, hats and sunglasses.
- Reapply at least every 2 hours.
- Use a water resistant sunscreen if swimming or sweating.
- Children under 6 months of age: Ask a doctor.

OTHER INFORMATION

- Protect the product in this container from excessive heat and direct sun.

INACTIVE INGREDIENTS

Caprylic/Capric Triglyceride, Castor Oil, Rosehip Oil, English Lavender Oil, Parsley Seed Oil, Sodium Hyaluronate, Candelilla Wax, Coco-Caprylate/
Caprate, Polyglyceryl-3 Polyricinoleate, Coconut Oil, Tocopheryl Acetate, Isostearic Acid, Linalool.